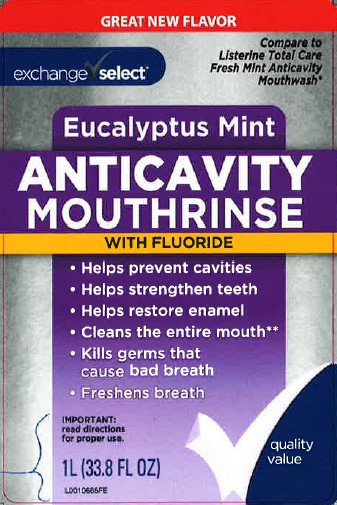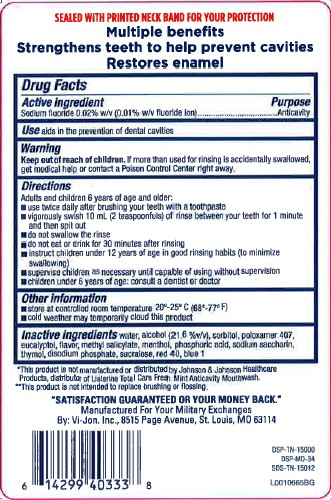 DRUG LABEL: Anticavity
NDC: 55301-163 | Form: MOUTHWASH
Manufacturer: Your Military Exchanges
Category: otc | Type: HUMAN OTC DRUG LABEL
Date: 20260212

ACTIVE INGREDIENTS: SODIUM FLUORIDE 0.1 mg/1 mL
INACTIVE INGREDIENTS: WATER; ALCOHOL; SORBITOL; POLOXAMER 407; EUCALYPTOL; METHYL SALICYLATE; MENTHOL; PHOSPHORIC ACID; SACCHARIN SODIUM; THYMOL; SODIUM PHOSPHATE, DIBASIC, ANHYDROUS; SUCRALOSE; FD&C RED NO. 40; FD&C BLUE NO. 1

Exchange Select 163.005/163AF-AG
Anticavity Fluoride Rinse

Tamper Evident Statement

SEALED WITH PRINTED NECKBAND FOR YOUR PROTECTION

Claims

Multiple benefits

Stengthens teeth to help prevent cavities

Restores enamel

Active ingredient

Sodium fluoride 0.02% w/v (0.01% w/v fluoride ion)

Purpose

Anticavity

Use

aids in the prevention of dental cavities

Warning

for this product

Keep out of reach of children.

If more than used for rinsing is accidentally swallowed, get medical help or contact a Poison Control Center right away.

Directions

Adults and children 6 years of age and older:

- use twice daily after brushing your teeth with a toothpaste
- vigorously swish 10 mL (2 teaspoonfuls) of rinse between your teeth for 1 minute and then spit out
- do not swallow the rinse
- do not eat or drink for 30 minutes after rinsing
- instruct children under 12 years of age in good rinsing habits (to minimize swallowing)
- supervise children as necessary until capable of using without supervision
- children under 6 years of age: consult a dentist or doctor

Other Information

- store at controlled room temperature 20⁰ -25⁰C (68⁰- 77⁰F)
- cold weather may temporarily cloud this product

Inactive ingredients

water, alcohol (21.6 %v/v), sorbitol, poloxamer 407, eucalyptol, flavor, methyl salicylate, menthol, phosphoric acid, sodium saccharin, thymol, disodium phosphate, sucralose, red 40, blue 1

Disclaimers

*This product is not manufactured or distributed by Johnson & Johnson Healthcare Products, distributor of Listerine® Total Care Fresh Mint Anticavity Mouthwash.

**This product is not intended to replace brushing or flossing

Adverse Reaction

"Satisfaction Guaranteed or Your Money Back."

Manufactured For Your Military Exchanges

By: Vi-Jon, LLC, 8515 Page Avenue, St. Louis, MO 63114

DSP-TN-15000

DSP-MO-34

SDS-TN-15012

Principal display panel

GREAT NEW FLAVOR

exchange Select™

Compare to Listerine Total Care Fresh Mint Anticavity Mouthwash*

Eucalyptus Mint

ANTICAVITY

MOUTHRINSE

WITH FLUORIDE

- Helps prevent cavities
- Helps strengthen teeth
- Helps restore enamel
- Cleans the entire mouth**
- Kills germs that cause bad breath
- Freshens breath

IMPORTANT: read directions for proper use.

quality value

1 L (33.8 FL OZ)